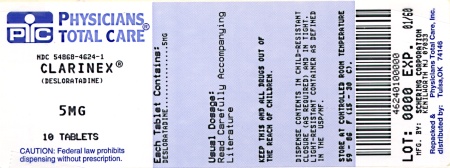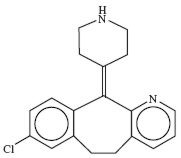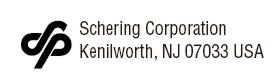 DRUG LABEL: Clarinex
NDC: 54868-4624 | Form: TABLET, FILM COATED
Manufacturer: Physicians Total Care, Inc.
Category: prescription | Type: HUMAN PRESCRIPTION DRUG LABEL
Date: 20101214

ACTIVE INGREDIENTS: DESLORATADINE 5 mg/1 1
INACTIVE INGREDIENTS: DIBASIC CALCIUM PHOSPHATE DIHYDRATE; CELLULOSE, MICROCRYSTALLINE; STARCH, CORN; TALC; CARNAUBA WAX; WHITE WAX; LACTOSE MONOHYDRATE; HYPROMELLOSES; TITANIUM DIOXIDE; POLYETHYLENE GLYCOL; FD&C BLUE NO. 2

DESCRIPTION

CLARINEX (desloratadine) Tablets are light blue, round, film coated tablets containing 5 mg desloratadine, an antihistamine, to be administered orally. It also contains the following excipients: dibasic calcium phosphate dihydrate USP, microcrystalline cellulose NF, corn starch NF, talc USP, carnauba wax NF, white wax NF, coating material consisting of lactose monohydrate, hypromellose, titanium dioxide, polyethylene glycol, and FD&C Blue #2 Aluminum Lake.

CLARINEX Syrup is a clear orange colored liquid containing 0.5 mg/1 mL desloratadine. The syrup contains the following inactive ingredients: propylene glycol USP, sorbitol solution USP, citric acid (anhydrous) USP, sodium citrate dihydrate USP, sodium benzoate NF, disodium edetate USP, purified water USP. It also contains granulated sugar, natural and artificial flavor for bubble gum and FD&C Yellow #6 dye.

The CLARINEX RediTabs® brand of desloratadine orally-disintegrating tablets are light red, flat-faced, round, speckled tablets with an "A" debossed on one side for the 5 mg tablets and a "K" debossed on one side for the 2.5 mg tablets. Each RediTabs Tablet contains either 5 mg or 2.5 mg of desloratadine. It also contains the following inactive ingredients: mannitol USP, microcrystalline cellulose NF, pregelatinized starch, NF, sodium starch glycolate, NF, magnesium stearate NF, butylated methacrylate copolymer, crospovidone, NF, aspartame NF, citric acid USP, sodium bicarbonate USP, colloidal silicon dioxide, NF, ferric oxide red NF and tutti frutti flavoring.

Desloratadine is a white to off-white powder that is slightly soluble in water, but very soluble in ethanol and propylene glycol. It has an empirical formula: C19H19ClN2 and a molecular weight of 310.8. The chemical name is 8-chloro-6,11-dihydro-11-(4-piperdinylidene)-5H-benzo[5,6]cyclohepta[1,2-b]pyridine and has the following structure:

CLINICAL PHARMACOLOGY

Mechanism of Action

Desloratadine is a long-acting tricyclic histamine antagonist with selective H1-receptor histamine antagonist activity. Receptor binding data indicate that at a concentration of 2–3 ng/mL (7 nanomolar), desloratadine shows significant interaction with the human histamine H1-receptor. Desloratadine inhibited histamine release from human mast cells in vitro.

Results of a radiolabeled tissue distribution study in rats and a radioligand H1-receptor binding study in guinea pigs showed that desloratadine did not readily cross the blood brain barrier.

Pharmacokinetics Absorption

Following oral administration of desloratadine 5 mg once daily for 10 days to normal healthy volunteers, the mean time to maximum plasma concentrations (Tmax) occurred at approximately 3 hours post dose and mean steady state peak plasma concentrations (Cmax) and area under the concentration-time curve (AUC) of 4 ng/mL and 56.9 ng∙hr/mL were observed, respectively. Neither food nor grapefruit juice had an effect on the bioavailability (Cmax and AUC) of desloratadine.

The pharmacokinetic profile of CLARINEX Syrup was evaluated in a three-way crossover study in 30 adult volunteers. A single dose of 10 mL of CLARINEX Syrup containing 5 mg of desloratadine was bioequivalent to a single dose of 5 mg CLARINEX Tablet. Food had no effect on the bioavailability (AUC and Cmax) of CLARINEX Syrup.

The pharmacokinetic profile of CLARINEX RediTabs Tablets was evaluated in a three-way crossover study in 24 adult volunteers. A single CLARINEX RediTabs Tablet containing 5 mg of desloratadine was bioequivalent to a single 5 mg CLARINEX RediTabs Tablet (original formulation) for both desloratadine and 3-hydroxydesloratadine. Water had no effect on the bioavailability (AUC and Cmax) of CLARINEX RediTabs Tablets.

Distribution

Desloratadine and 3-hydroxydesloratadine are approximately 82% to 87% and 85% to 89%, bound to plasma proteins, respectively. Protein binding of desloratadine and 3-hydroxydesloratadine was unaltered in subjects with impaired renal function.

Metabolism

Desloratadine (a major metabolite of loratadine) is extensively metabolized to 3-hydroxydesloratadine, an active metabolite, which is subsequently glucuronidated. The enzyme(s) responsible for the formation of 3-hydroxydesloratadine have not been identified. Data from clinical trials indicate that a subset of the general population has a decreased ability to form 3-hydroxydesloratadine, and are poor metabolizers of desloratadine. In pharmacokinetic studies (n=3748), approximately 6% of subjects were poor metabolizers of desloratadine (defined as a subject with an AUC ratio of 3-hydroxydesloratadine to desloratadine less than 0.1, or a subject with a desloratadine half-life exceeding 50 hours). These pharmacokinetic studies included subjects between the ages of 2 and 70 years, including 977 subjects aged 2–5 years, 1575 subjects aged 6–11 years, and 1196 subjects aged 12–70 years. There was no difference in the prevalence of poor metabolizers across age groups. The frequency of poor metabolizers was higher in Blacks (17%, n=988) as compared to Caucasians (2%, n=1462) and Hispanics (2%, n=1063). The median exposure (AUC) to desloratadine in the poor metabolizers was approximately 6-fold greater than in the subjects who are not poor metabolizers. Subjects who are poor metabolizers of desloratadine cannot be prospectively identified and will be exposed to higher levels of desloratadine following dosing with the recommended dose of desloratadine. In multidose clinical safety studies, where metabolizer status was identified, a total of 94 poor metabolizers and 123 normal metabolizers were enrolled and treated with CLARINEX Syrup for 15–35 days. In these studies, no overall differences in safety were observed between poor metabolizers and normal metabolizers. Although not seen in these studies, an increased risk of exposure-related adverse events in patients who are poor metabolizers cannot be ruled out.

Elimination

The mean elimination half-life of desloratadine was 27 hours. Cmax and AUC values increased in a dose proportional manner following single oral doses between 5 and 20 mg. The degree of accumulation after 14 days of dosing was consistent with the half-life and dosing frequency. A human mass balance study documented a recovery of approximately 87% of the ^14C-desloratadine dose, which was equally distributed in urine and feces as metabolic products. Analysis of plasma 3-hydroxydesloratadine showed similar Tmax and half-life values compared to desloratadine.

Special Populations Geriatric

In older subjects (> 65 years old; n=17) following multiple-dose administration of CLARINEX Tablets, the mean Cmax and AUC values for desloratadine were 20% greater than in younger subjects (< 65 years old). The oral total body clearance (CL/F) when normalized for body weight was similar between the two age groups. The mean plasma elimination half-life of desloratadine was 33.7 hr in subjects > 65 years old. The pharmacokinetics for 3-hydroxydesloratadine appeared unchanged in older versus younger subjects. These age-related differences are unlikely to be clinically relevant and no dosage adjustment is recommended in elderly subjects.

Pediatric Subjects

In subjects 6 to 11 years old, a single dose of 5 mL of CLARINEX Syrup containing 2.5 mg of desloratadine resulted in desloratadine plasma concentrations similar to those achieved in adults administered a single 5 mg CLARINEX Tablet. In subjects 2 to 5 years old, a single dose of 2.5 mL of CLARINEX Syrup containing 1.25 mg of desloratadine resulted in desloratadine plasma concentrations similar to those achieved in adults administered a single 5 mg CLARINEX Tablet. However, the Cmax and AUCt of the metabolite (3-OH desloratadine) were 1.27 and 1.61 times higher for the 5 mg dose of syrup administered in adults compared to the Cmax and AUCt obtained in children 2–11 years of age receiving 1.25–2.5 mg of CLARINEX Syrup.

A single dose of either 2.5 mL or 1.25 mL of CLARINEX Syrup containing 1.25 mg or 0.625 mg, respectively, of desloratadine was administered to subjects 6 to 11 months of age and 12 to 23 months of age. The results of a population pharmacokinetic analysis indicated that a dose of 1 mg for subjects aged 6 to 11 months and 1.25 mg for subjects 12 to 23 months of age is required to obtain desloratadine plasma concentrations similar to those achieved in adults administered a single 5 mg dose of CLARINEX Syrup.

The CLARINEX RediTabs Tablet 2.5 mg tablet has not been evaluated in pediatric patients. Bioequivalence of the CLARINEX RediTabs Tablet and the original CLARINEX RediTabs Tablets was established in adults. In conjunction with the dose finding studies in pediatrics described, the pharmacokinetic data for CLARINEX RediTabs Tablet supports the use of the 2.5 mg dose strength in pediatric patients 6–11 years of age.

Renally Impaired

Desloratadine pharmacokinetics following a single dose of 7.5 mg were characterized in patients with mild (n=7; creatinine clearance 51–69 mL/min/1.73 m^2), moderate (n=6; creatinine clearance 34–43 mL/min/1.73 m^2), and severe (n=6; creatinine clearance 5–29 mL/min/1.73 m^2) renal impairment or hemodialysis-dependent (n=6) patients. In patients with mild and moderate renal impairment, median Cmax and AUC values increased by approximately 1.2- and 1.9-fold, respectively, relative to subjects with normal renal function. In patients with severe renal impairment or who were hemodialysis dependent, Cmax and AUC values increased by approximately 1.7- and 2.5-fold, respectively. Minimal changes in 3-hydroxydesloratadine concentrations were observed. Desloratadine and 3-hydroxydesloratadine were poorly removed by hemodialysis. Plasma protein binding of desloratadine and 3-hydroxydesloratadine was unaltered by renal impairment. Dosage adjustment for patients with renal impairment is recommended (see DOSAGE AND ADMINISTRATION section).

Hepatically Impaired

Desloratadine pharmacokinetics were characterized following a single oral dose in patients with mild (n=4), moderate (n=4), and severe (n=4) hepatic impairment as defined by the Child-Pugh classification of hepatic function and 8 subjects with normal hepatic function. Patients with hepatic impairment, regardless of severity, had approximately a 2.4-fold increase in AUC as compared with normal subjects. The apparent oral clearance of desloratadine in patients with mild, moderate, and severe hepatic impairment was 37%, 36%, and 28% of that in normal subjects, respectively. An increase in the mean elimination half-life of desloratadine in patients with hepatic impairment was observed. For 3-hydroxydesloratadine, the mean Cmax and AUC values for patients with hepatic impairment were not statistically significantly different from subjects with normal hepatic function. Dosage adjustment for patients with hepatic impairment is recommended (see DOSAGE AND ADMINISTRATION section).

Gender

Female subjects treated for 14 days with CLARINEX Tablets had 10% and 3% higher desloratadine Cmax and AUC values, respectively, compared with male subjects. The 3-hydroxydesloratadine Cmax and AUC values were also increased by 45% and 48%, respectively, in females compared with males. However, these apparent differences are not likely to be clinically relevant and therefore no dosage adjustment is recommended.

Race

Following 14 days of treatment with CLARINEX Tablets, the Cmax and AUC values for desloratadine were 18% and 32% higher, respectively, in Blacks compared with Caucasians. For 3-hydroxydesloratadine there was a corresponding 10% reduction in Cmax and AUC values in Blacks compared to Caucasians. These differences are not likely to be clinically relevant and therefore no dose adjustment is recommended.

Drug Interactions

In two controlled crossover clinical pharmacology studies in healthy male (n=12 in each study) and female (n=12 in each study) volunteers, desloratadine 7.5 mg (1.5 times the daily dose) once daily was coadministered with erythromycin 500 mg every 8 hours or ketoconazole 200 mg every 12 hours for 10 days. In three separate controlled, parallel group clinical pharmacology studies, desloratadine at the clinical dose of 5 mg has been coadministered with azithromycin 500 mg followed by 250 mg once daily for 4 days (n=18) or with fluoxetine 20 mg once daily for 7 days after a 23-day pretreatment period with fluoxetine (n=18) or with cimetidine 600 mg every 12 hours for 14 days (n=18) under steady state conditions to normal healthy male and female volunteers. Although increased plasma concentrations (Cmax and AUC 0–24 hrs) of desloratadine and 3-hydroxydesloratadine were observed (see Table 1), there were no clinically relevant changes in the safety profile of desloratadine, as assessed by electrocardiographic parameters (including the corrected QT interval), clinical laboratory tests, vital signs, and adverse events.

Table 1 Changes in Desloratadine and 3-Hydroxydesloratadine Pharmacokinetics in Healthy Male and Female Volunteers
 | Desloratadine |  | 3-Hydroxydesloratadine
 | Cmax | AUC 0–24 hrs | Cmax | AUC 0–24 hrs
Erythromycin (500 mg Q8h) | +24% | +14% | +43% | +40%
Ketoconazole (200 mg Q12h) | +45% | +39% | +43% | +72%
Azithromycin (500 mg day 1, 250 mg QD × 4 days) | +15% | +5% | +15% | +4%
Fluoxetine (20 mg QD) | +15% | +0% | +17% | +13%
Cimetidine (600 mg Q12h) | +12% | +19% | -11% | -3%

Pharmacodynamics Wheal and Flare

Human histamine skin wheal studies following single and repeated 5 mg doses of desloratadine have shown that the drug exhibits an antihistaminic effect by 1 hour; this activity may persist for as long as 24 hours. There was no evidence of histamine-induced skin wheal tachyphylaxis within the desloratadine 5 mg group over the 28-day treatment period. The clinical relevance of histamine wheal skin testing is unknown.

Effects on QTc

Single dose administration of desloratadine did not alter the corrected QT interval (QTc) in rats (up to 12 mg/kg, oral), or guinea pigs (25 mg/kg, intravenous). Repeated oral administration at doses up to 24 mg/kg for durations up to 3 months in monkeys did not alter the QTc at an estimated desloratadine exposure (AUC) that was approximately 955 times the mean AUC in humans at the recommended daily oral dose. See OVERDOSAGE section for information on human QTc experience.

Clinical Trials Seasonal Allergic Rhinitis

The clinical efficacy and safety of CLARINEX Tablets were evaluated in over 2,300 patients 12 to 75 years of age with seasonal allergic rhinitis. A total of 1,838 patients received 2.5–20 mg/day of CLARINEX in four double-blind, randomized, placebo-controlled clinical trials of 2 to 4 weeks' duration conducted in the United States. The results of these studies demonstrated the efficacy and safety of CLARINEX 5 mg in the treatment of adult and adolescent patients with seasonal allergic rhinitis. In a dose ranging trial, CLARINEX 2.5–20 mg/day was studied. Doses of 5, 7.5, 10, and 20 mg/day were superior to placebo; and no additional benefit was seen at doses above 5.0 mg. In the same study, an increase in the incidence of somnolence was observed at doses of 10 mg/day and 20 mg/day (5.2% and 7.6%, respectively), compared to placebo (2.3%).

In two 4-week studies of 924 patients (aged 15 to 75 years) with seasonal allergic rhinitis and concomitant asthma, CLARINEX Tablets 5 mg once daily improved rhinitis symptoms, with no decrease in pulmonary function. This supports the safety of administering CLARINEX Tablets to adult patients with seasonal allergic rhinitis with mild to moderate asthma.

CLARINEX Tablets 5 mg once daily significantly reduced the Total Symptom Scores (the sum of individual scores of nasal and non-nasal symptoms) in patients with seasonal allergic rhinitis. See Table 2.

Table 2 TOTAL SYMPTOM SCORE (TSS) Changes in a 2-Week Clinical Trial in Patients with Seasonal Allergic Rhinitis
Treatment Group (n) | Mean Baseline* (sem) | Change from Baseline† (sem) | Placebo Comparison (P-value)
CLARINEX 5.0 mg (171) | 14.2 (0.3) | -4.3 (0.3) | P<0.01
Placebo (173) | 13.7 (0.3) | -2.5 (0.3)

*At baseline, a total nasal symptom score (sum of 4 individual symptoms) of at least 6 and a total non-nasal symptom score (sum of 4 individual symptoms) of at least 5 (each symptom scored 0 to 3 where 0=no symptom and 3=severe symptoms) was required for trial eligibility. TSS ranges from 0=no symptoms to 24=maximal symptoms.†Mean reduction in TSS averaged over the 2-week treatment period.

There were no significant differences in the effectiveness of CLARINEX Tablets 5 mg across subgroups of patients defined by gender, age, or race.

Perennial Allergic Rhinitis

The clinical efficacy and safety of CLARINEX Tablets 5 mg were evaluated in over 1,300 patients 12 to 80 years of age with perennial allergic rhinitis. A total of 685 patients received 5 mg/day of CLARINEX in two double-blind, randomized, placebo-controlled clinical trials of 4 weeks' duration conducted in the United States and internationally. In one of these studies CLARINEX Tablets 5 mg once daily was shown to significantly reduce symptoms of perennial allergic rhinitis (Table 3).

Table 3 TOTAL SYMPTOM SCORE (TSS) Changes in a 4-Week Clinical Trial in Patients with Perennial Allergic Rhinitis
Treatment Group (n) | Mean Baseline* (sem) | Change from Baseline† (sem) | Placebo Comparison (P-value)
CLARINEX 5.0 mg (337) | 12.37 (0.18) | -4.06 (0.21) | P=0.01
Placebo (337) | 12.30 (0.18) | -3.27 (0.21)

*At baseline, average of total symptom score (sum of 5 individual nasal symptoms and 3 non-nasal symptoms, each symptom scored 0 to 3 where 0=no symptom and 3=severe symptoms) of at least 10 was required for trial eligibility. TSS ranges from 0=no symptoms to 24=maximal symptoms.†Mean reduction in TSS averaged over the 4-week treatment period.

Chronic Idiopathic Urticaria

The efficacy and safety of CLARINEX Tablets 5 mg once daily was studied in 416 chronic idiopathic urticaria patients 12 to 84 years of age, of whom 211 received CLARINEX. In two double-blind, placebo-controlled, randomized clinical trials of six weeks' duration, at the pre-specified one-week primary time point evaluation, CLARINEX Tablets significantly reduced the severity of pruritus when compared to placebo (Table 4). Secondary endpoints were also evaluated and during the first week of therapy CLARINEX Tablets 5 mg reduced the secondary endpoints, "Number of Hives" and the "Size of the Largest Hive," when compared to placebo.

Table 4 PRURITUS SYMPTOM SCORE Changes in the First Week of a Clinical Trial in Patients with Chronic Idiopathic Urticaria
Treatment Group (n) | Mean Baseline (sem) | Change from Baseline* (sem) | Placebo Comparison (P-value)
CLARINEX 5.0 mg (115) | 2.19 (0.04) | -1.05 (0.07) | P<0.01
Placebo (110) | 2.21 (0.04) | -0.52 (0.07)

Pruritus scored 0 to 3 where 0=no symptom to 3=maximal symptom.

*Mean reduction in pruritus averaged over the first week of treatment.

The clinical safety of CLARINEX Syrup was documented in three, 15-day, double-blind, placebo-controlled safety studies in pediatric subjects with a documented history of allergic rhinitis, chronic idiopathic urticaria, or subjects who were candidates for antihistamine therapy. In the first study, 2.5 mg of CLARINEX Syrup was administered to 60 pediatric subjects 6 to 11 years of age. The second study evaluated 1.25 mg of CLARINEX Syrup administered to 55 pediatric subjects 2 to 5 years of age. In the third study, 1.25 mg of CLARINEX Syrup was administered to 65 pediatric subjects 12 to 23 months of age and 1.0 mg of CLARINEX Syrup was administered to 66 pediatric subjects 6 to 11 months of age. The results of these studies demonstrated the safety of CLARINEX Syrup in pediatric subjects 6 months to 11 years of age.

INDICATIONS AND USAGE

Seasonal Allergic Rhinitis

CLARINEX is indicated for the relief of the nasal and non-nasal symptoms of seasonal allergic rhinitis in patients 2 years of age and older.

Perennial Allergic Rhinitis

CLARINEX is indicated for the relief of the nasal and non-nasal symptoms of perennial allergic rhinitis in patients 6 months of age and older.

Chronic Idiopathic Urticaria

CLARINEX is indicated for the symptomatic relief of pruritus, reduction in the number of hives, and size of hives, in patients with chronic idiopathic urticaria 6 months of age and older.

CONTRAINDICATIONS

CLARINEX Tablets 5 mg are contraindicated in patients who are hypersensitive to this medication or to any of its ingredients, or to loratadine.

PRECAUTIONS

Carcinogenesis, Mutagenesis, Impairment of Fertility

The carcinogenic potential of desloratadine was assessed using a loratadine study in rats and a desloratadine study in mice. In a 2-year study in rats, loratadine was administered in the diet at doses up to 25 mg/kg/day (estimated desloratadine and desloratadine metabolite exposures were approximately 30 times the AUC in humans at the recommended daily oral dose). A significantly higher incidence of hepatocellular tumors (combined adenomas and carcinomas) was observed in males given 10 mg/kg/day of loratadine and in males and females given 25 mg/kg/day of loratadine. The estimated desloratadine and desloratadine metabolite exposures in rats given 10 mg/kg of loratadine were approximately 7 times the AUC in humans at the recommended daily oral dose. The clinical significance of these findings during long-term use of desloratadine is not known.

In a 2-year dietary study in mice, males and females given up to 16 mg/kg/day and 32 mg/kg/day desloratadine, respectively, did not show significant increases in the incidence of any tumors. The estimated desloratadine and metabolite exposures in mice at these doses were 12 and 27 times, respectively, the AUC in humans at the recommended daily oral dose.

In genotoxicity studies with desloratadine, there was no evidence of genotoxic potential in a reverse mutation assay (Salmonella/E. coli mammalian microsome bacterial mutagenicity assay) or in two assays for chromosomal aberrations (human peripheral blood lymphocyte clastogenicity assay and mouse bone marrow micronucleus assay).

There was no effect on female fertility in rats at desloratadine doses up to 24 mg/kg/day (estimated desloratadine and desloratadine metabolite exposures were approximately 130 times the AUC in humans at the recommended daily oral dose). A male specific decrease in fertility, demonstrated by reduced female conception rates, decreased sperm numbers and motility, and histopathologic testicular changes, occurred at an oral desloratadine dose of 12 mg/kg in rats (estimated desloratadine exposures were approximately 45 times the AUC in humans at the recommended daily oral dose). Desloratadine had no effect on fertility in rats at an oral dose of 3 mg/kg/day (estimated desloratadine and desloratadine metabolite exposures were approximately 8 times the AUC in humans at the recommended daily oral dose).

Pregnancy Category C

Desloratadine was not teratogenic in rats at doses up to 48 mg/kg/day (estimated desloratadine and desloratadine metabolite exposures were approximately 210 times the AUC in humans at the recommended daily oral dose) or in rabbits at doses up to 60 mg/kg/day (estimated desloratadine exposures were approximately 230 times the AUC in humans at the recommended daily oral dose). In a separate study, an increase in pre-implantation loss and a decreased number of implantations and fetuses were noted in female rats at 24 mg/kg (estimated desloratadine and desloratadine metabolite exposures were approximately 120 times the AUC in humans at the recommended daily oral dose). Reduced body weight and slow righting reflex were reported in pups at doses of 9 mg/kg/day or greater (estimated desloratadine and desloratadine metabolite exposures were approximately 50 times or greater than the AUC in humans at the recommended daily oral dose). Desloratadine had no effect on pup development at an oral dose of 3 mg/kg/day (estimated desloratadine and desloratadine metabolite exposures were approximately 7 times the AUC in humans at the recommended daily oral dose). There are, however, no adequate and well-controlled studies in pregnant women. Because animal reproduction studies are not always predictive of human response, desloratadine should be used during pregnancy only if clearly needed.

Nursing Mothers

Desloratadine passes into breast milk; therefore a decision should be made whether to discontinue nursing or to discontinue desloratadine, taking into account the importance of the drug to the mother.

Pediatric Use

The recommended dose of CLARINEX Syrup in the pediatric population is based on cross-study comparison of the plasma concentration of CLARINEX in adults and pediatric subjects. The safety of CLARINEX Syrup has been established in 246 pediatric subjects aged 6 months to 11 years in three placebo-controlled clinical studies. Since the course of seasonal and perennial allergic rhinitis and chronic idiopathic urticaria and the effects of CLARINEX are sufficiently similar in the pediatric and adult populations, it allows extrapolation from the adult efficacy data to pediatric patients. The effectiveness of CLARINEX Syrup in these age groups is supported by evidence from adequate and well-controlled studies of CLARINEX Tablets in adults. The safety and effectiveness of CLARINEX Tablets or CLARINEX Syrup have not been demonstrated in pediatric patients less than 6 months of age.

The CLARINEX RediTabs Tablet 2.5 mg tablet has not been evaluated in pediatric patients. Bioequivalence of the CLARINEX RediTabs Tablet and the previously marketed RediTabs Tablet was established in adults. In conjunction with the dose finding studies in pediatrics described, the pharmacokinetic data for CLARINEX RediTabs Tablet supports the use of the 2.5 mg dose strength in pediatric patients 6–11 years of age.

Geriatric Use

Clinical studies of desloratadine did not include sufficient numbers of subjects aged 65 and over to determine whether they respond differently from younger subjects. Other reported clinical experience has not identified differences between the elderly and younger patients. In general, dose selection for an elderly patient should be cautious, reflecting the greater frequency of decreased hepatic, renal, or cardiac function, and of concomitant disease or other drug therapy (see CLINICAL PHARMACOLOGY – Special Populations).

Information for Patients

Patients should be instructed to use CLARINEX Tablets as directed. As there are no food effects on bioavailability, patients can be instructed that CLARINEX Tablets, Syrup, or RediTabs Tablets may be taken without regard to meals. Patients should be advised not to increase the dose or dosing frequency, as studies have not demonstrated increased effectiveness at higher doses and somnolence may occur. Phenylketonurics: CLARINEX RediTabs Tablets contain phenylalanine 2.9 mg per 5 mg CLARINEX RediTabs Tablet or 1.4 mg per 2.5 mg CLARINEX RediTabs Tablet.

ADVERSE REACTIONS

Adults and Adolescents Allergic Rhinitis

In multiple-dose placebo-controlled trials, 2,834 patients ages 12 years or older received CLARINEX Tablets at doses of 2.5 mg to 20 mg daily, of whom 1,655 patients received the recommended daily dose of 5 mg. In patients receiving 5 mg daily, the rate of adverse events was similar between CLARINEX and placebo-treated patients. The percent of patients who withdrew prematurely due to adverse events was 2.4% in the CLARINEX group and 2.6% in the placebo group. There were no serious adverse events in these trials in patients receiving desloratadine. All adverse events that were reported by greater than or equal to 2% of patients who received the recommended daily dose of CLARINEX Tablets (5.0 mg once-daily), and that were more common with CLARINEX Tablets than placebo, are listed in Table 5.

Table 5 Incidence of Adverse Events Reported by 2% or More of Adult and Adolescent Allergic Rhinitis Patients in Placebo-Controlled, Multiple-Dose Clinical Trials with the Tablet Formulation of CLARINEX
Adverse Experience | CLARINEX Tablets 5 mg (n=1,655) | Placebo (n=1,652)
Pharyngitis | 4.1% | 2.0%
Dry Mouth | 3.0% | 1.9%
Myalgia | 2.1% | 1.8%
Fatigue | 2.1% | 1.2%
Somnolence | 2.1% | 1.8%
Dysmenorrhea | 2.1% | 1.6%

The frequency and magnitude of laboratory and electrocardiographic abnormalities were similar in CLARINEX and placebo-treated patients.

There were no differences in adverse events for subgroups of patients as defined by gender, age, or race.

Chronic Idiopathic Urticaria

In multiple-dose, placebo-controlled trials of chronic idiopathic urticaria, 211 patients ages 12 years or older received CLARINEX Tablets and 205 received placebo. Adverse events that were reported by greater than or equal to 2% of patients who received CLARINEX Tablets and that were more common with CLARINEX than placebo were (rates for CLARINEX and placebo, respectively): headache (14%, 13%), nausea (5%, 2%), fatigue (5%, 1%), dizziness (4%, 3%), pharyngitis (3%, 2%), dyspepsia (3%, 1%), and myalgia (3%, 1%).

Pediatrics

Two hundred and forty-six pediatric subjects 6 months to 11 years of age received CLARINEX Syrup for 15 days in three placebo-controlled clinical trials. Pediatric subjects aged 6 to 11 years received 2.5 mg once a day, subjects aged 1 to 5 years received 1.25 mg once a day, and subjects 6 to 11 months of age received 1.0 mg once a day. In subjects 6 to 11 years of age, no individual adverse event was reported by 2 percent or more of the subjects. In subjects 2 to 5 years of age, adverse events reported for CLARINEX and placebo in at least 2 percent of subjects receiving CLARINEX Syrup and at a frequency greater than placebo were fever (5.5%, 5.4%), urinary tract infection (3.6%, 0%), and varicella (3.6%, 0%). In subjects 12 months to 23 months of age, adverse events reported for the CLARINEX product and placebo in at least 2 percent of subjects receiving CLARINEX Syrup and at a frequency greater than placebo were fever (16.9%, 12.9%), diarrhea (15.4%, 11.3%), upper respiratory tract infections (10.8%, 9.7%), coughing (10.8%, 6.5%), appetite increased (3.1%, 1.6%), emotional lability (3.1%, 0%), epistaxis (3.1%, 0%), parasitic infection (3.1%, 0%), pharyngitis (3.1%, 0%), rash maculopapular (3.1%, 0%). In subjects 6 months to 11 months of age, adverse events reported for CLARINEX and placebo in at least 2 percent of subjects receiving CLARINEX Syrup and at a frequency greater than placebo were upper respiratory tract infections (21.2%, 12.9%), diarrhea (19.7%, 8.1%), fever (12.1%, 1.6%), irritability (12.1%, 11.3%), coughing (10.6%, 9.7%), somnolence (9.1%, 8.1%), bronchitis (6.1%, 0%), otitis media (6.1%, 1.6%), vomiting (6.1%, 3.2%), anorexia (4.5%, 1.6%), pharyngitis (4.5%, 1.6%), insomnia (4.5%, 0%), rhinorrhea (4.5%, 3.2%), erythema (3.0%, 1.6%), and nausea (3.0%, 0%). There were no clinically meaningful changes in any electrocardiographic parameter, including the QTc interval. Only one of the 246 pediatric subjects receiving CLARINEX Syrup in the clinical trials discontinued treatment because of an adverse event.

Observed During Clinical Practice

The following spontaneous adverse events have been reported during the marketing of desloratadine: tachycardia, palpitations, rare cases of hypersensitivity reactions (such as rash, pruritus, urticaria, edema, dyspnea, and anaphylaxis), psychomotor hyperactivity, seizures, and elevated liver enzymes including bilirubin, and very rarely, hepatitis.

DRUG ABUSE AND DEPENDENCE

There is no information to indicate that abuse or dependency occurs with CLARINEX Tablets.

OVERDOSAGE

Information regarding acute overdosage is limited to experience from clinical trials conducted during the development of the CLARINEX product. In a dose ranging trial, at doses of 10 mg and 20 mg/day somnolence was reported.

Single daily doses of 45 mg were given to normal male and female volunteers for 10 days. All ECGs obtained in this study were manually read in a blinded fashion by a cardiologist. In CLARINEX-treated subjects, there was an increase in mean heart rate of 9.2 bpm relative to placebo. The QT interval was corrected for heart rate (QTc) by both the Bazett and Fridericia methods. Using the QTc (Bazett) there was a mean increase of 8.1 msec in CLARINEX-treated subjects relative to placebo. Using QTc (Fridericia) there was a mean increase of 0.4 msec in CLARINEX-treated subjects relative to placebo. No clinically relevant adverse events were reported.

In the event of overdose, consider standard measures to remove any unabsorbed drug. Symptomatic and supportive treatment is recommended. Desloratadine and 3-hydroxy-desloratadine are not eliminated by hemodialysis.

Lethality occurred in rats at oral doses of 250 mg/kg or greater (estimated desloratadine and desloratadine metabolite exposures were approximately 120 times the AUC in humans at the recommended daily oral dose). The oral median lethal dose in mice was 353 mg/kg (estimated desloratadine exposures were approximately 290 times the human daily oral dose on a mg/m^2 basis). No deaths occurred at oral doses up to 250 mg/kg in monkeys (estimated desloratadine exposures were approximately 810 times the human daily oral dose on a mg/m^2 basis).

DOSAGE AND ADMINISTRATION

Adults and children 12 years of age and over

The recommended dose of CLARINEX Tablets or CLARINEX RediTabs Tablets is one 5 mg tablet once daily or the recommended dose of CLARINEX Syrup is 2 teaspoonfuls (5 mg in 10 mL) once daily.

Children 6 to 11 years of age

The recommended dose of CLARINEX Syrup is 1 teaspoonful (2.5 mg in 5 mL) once daily or the recommended dose of CLARINEX RediTabs Tablets is one 2.5 mg tablet once daily.

Children 12 months to 5 years of age

The recommended dose of CLARINEX Syrup is ½ teaspoonful (1.25 mg in 2.5 mL) once daily.

Children 6 to 11 months of age

The recommended dose of CLARINEX Syrup is 2 mL (1.0 mg) once daily.

The age-appropriate dose of CLARINEX Syrup should be administered with a commercially available measuring dropper or syringe that is calibrated to deliver 2 mL and 2.5 mL (½ teaspoon).

In adult patients with liver or renal impairment, a starting dose of one 5 mg tablet every other day is recommended based on pharmacokinetic data. Dosing recommendation for children with liver or renal impairment cannot be made due to lack of data.

Administration of CLARINEX RediTabs Tablets

Place CLARINEX (desloratadine) RediTabs Tablets on the tongue and allow to disintegrate before swallowing. Tablet disintegration occurs rapidly. Administer with or without water. Take tablet immediately after opening the blister.

HOW SUPPLIED

CLARINEX Tablets

Embossed "C5", light blue film coated tablets; that are packaged in

plastic bottles of 10 | NDC 54868-4624-1
Unit-of-Use package of 30 tablets (3 x 10; 10 blisters per card) | NDC 54868-4624-0

Protect Unit-of-Use packaging from excessive moisture.

Store at 25°C (77°F); excursions permitted to 15°–30°C (59°–86°F) [see USP Controlled Room Temperature]. Heat sensitive. Avoid exposure at or above 30°C (86°F).

Rev. 2/07
23882191T

U.S. Patent Nos. 4,659,716; 4,863,931; 5,178,878; 5,607,697; 6,100,274; 6,514,520; 6,709,676; and 6,979,463.

Copyright © 2004, 2005, Schering Corporation. All rights reserved.

Relabeling and Repackaging by:
Physicians Total Care, Inc.
Tulsa, OK 74146

PRINCIPAL DISPLAY PANEL

CLARINEX (desloratadine) Tablets